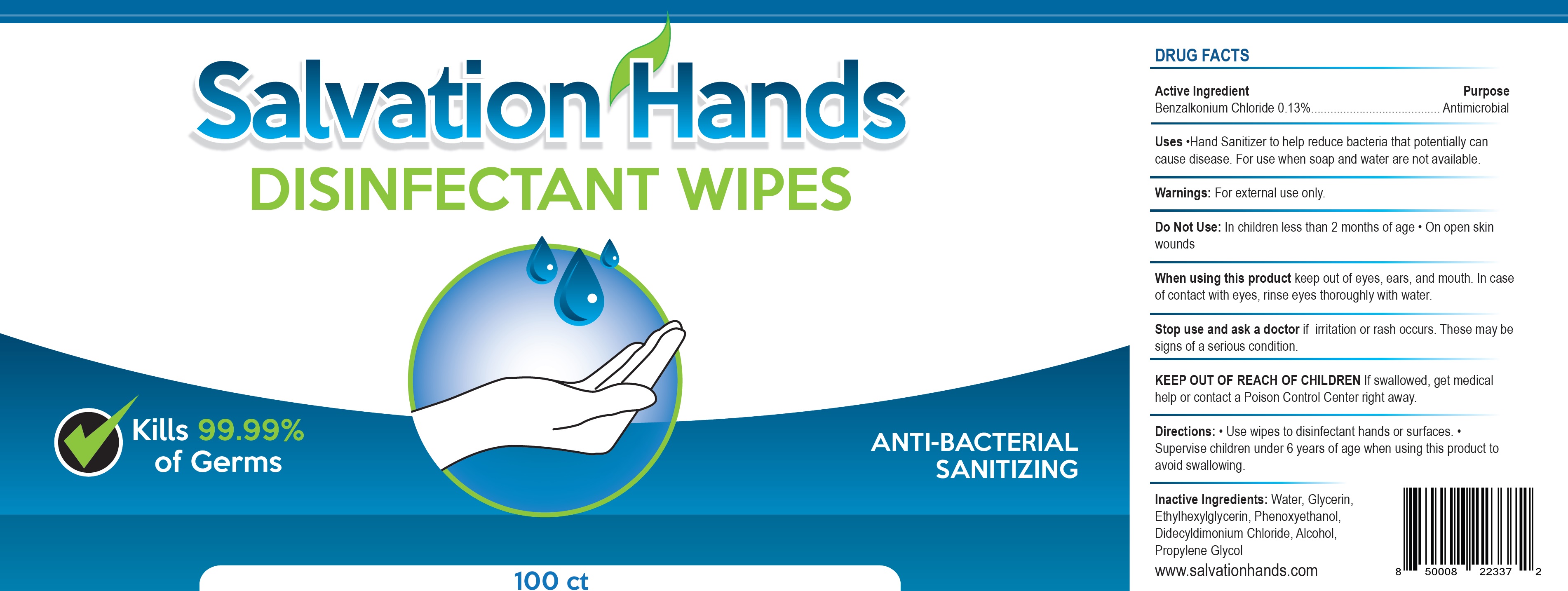 DRUG LABEL: Salvation Hands Disinfectant Wipes
NDC: 79915-001 | Form: CLOTH
Manufacturer: E-Liquids Investment Group LLC
Category: otc | Type: HUMAN OTC DRUG LABEL
Date: 20201119

ACTIVE INGREDIENTS: BENZALKONIUM CHLORIDE 1.3 mg/1 mL
INACTIVE INGREDIENTS: WATER; GLYCERIN; ETHYLHEXYLGLYCERIN; PHENOXYETHANOL; DIDECYLDIMONIUM CHLORIDE; ALCOHOL; PROPYLENE GLYCOL

Salvation Hands Disinfectant Wipes

Active Ingredient

Benzalkonium Chloride 0.13%

Purpose

Antimicrobial

Uses

- Hand Sanitizer to help reduce bacteria that potentially can cause disease. For use when soap and water are not available.

Warnings:

For external use only.

Do Not Use:

In children less than 2 months of age

- On open skin wounds

When using this product

keep out of eyes, ears, and mouth. In case of contact with eyes, rinse eyes thoroughly with water.

Stop use and ask a doctor

if irritation or rash occurs. These may be signs of a serious condition.

KEEP OUT OF REACH OF CHILDREN

If swallowed, get medical help or contact a Poison Control Center right away.

Directions:

- Use wipes to disinfectant hands or surfaces.
- Supervise children under 6 years of age when using this product to avoid swallowing.

Inactive Ingredients:

Water, Glycerin, Ethylhexylglycerin, Phenoxyethanol, Didecyldimonium Chloride, Alcohol, Propylene Glycol
www.salvationhands.com